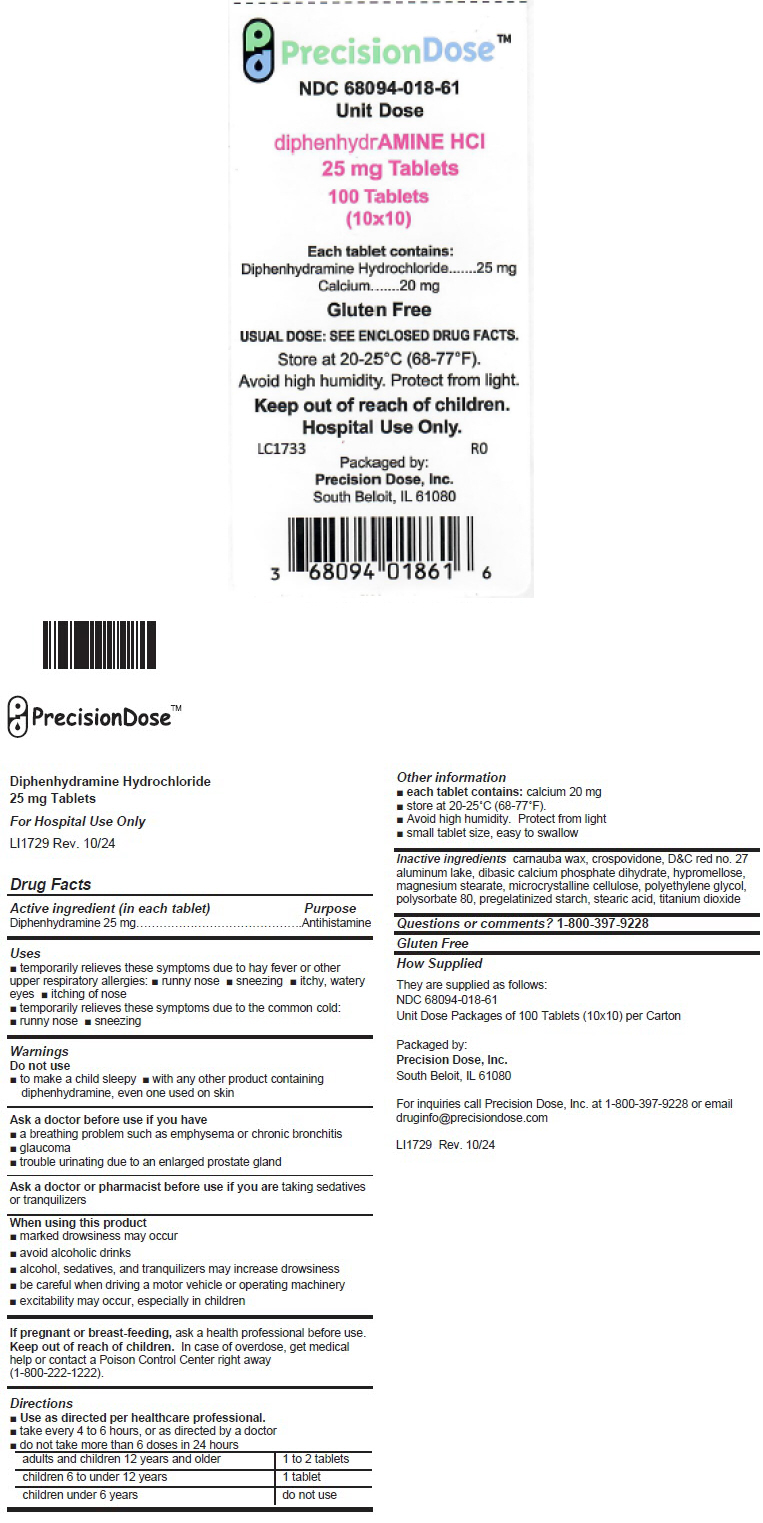 DRUG LABEL: Diphenhydramine Hydrochloride
NDC: 68094-018 | Form: TABLET
Manufacturer: Precision Dose, Inc.
Category: otc | Type: HUMAN OTC DRUG LABEL
Date: 20250912

ACTIVE INGREDIENTS: diphenhydramine hydrochloride 25 mg/1 1
INACTIVE INGREDIENTS: carnauba wax; crospovidone (120 .MU.M); D&C Red No. 27; HYPROMELLOSE, UNSPECIFIED; Magnesium Stearate; MICROCRYSTALLINE CELLULOSE; POLYETHYLENE GLYCOL, UNSPECIFIED; Polysorbate 80; STEARIC ACID; Titanium dioxide; anhydrous dibasic calcium phosphate

Diphenhydramine Hydrochloride

25 mg Tablets

For Hospital Use Only

LI1729 Rev. 10/24

Drug Facts

Active ingredient (in each tablet)

Diphenhydramine 25 mg

Purpose

Antihistamine

Uses

- temporarily relieves these symptoms due to hay fever or other upper respiratory allergies:
  - runny nose
  - sneezing
  - itchy, watery eyes
  - itching of nose
- temporarily relieves these symptoms due to the common cold:
  - runny nose
  - sneezing

Warnings

Do not use

- to make a child sleepy
- with any other product containing diphenhydramine, even one used on skin

Ask a doctor before use if you have

- a breathing problem such as emphysema or chronic bronchitis
- glaucoma
- trouble urinating due to an enlarged prostate gland

Ask a doctor or pharmacist before use if you are taking sedatives or tranquilizers

When using this product

- marked drowsiness may occur
- avoid alcoholic drinks
- alcohol, sedatives, and tranquilizers may increase drowsiness
- be careful when driving a motor vehicle or operating machinery
- excitability may occur, especially in children

PREGNANCY OR BREAST FEEDING

If pregnant or breast-feeding, ask a health professional before use.

Keep out of reach of children. In case of overdose, get medical help or contact a Poison Control Center right away (1-800-222-1222).

Directions

- Use as directed per healthcare professional.
- take every 4 to 6 hours, or as directed by a doctor
- do not take more than 6 doses in 24 hours

adults and children 12 years and older | 1 to 2 tablets
children 6 to under 12 years | 1 tablet
children under 6 years | do not use

Other information

- each tablet contains: calcium 20 mg
- store at 20-25°C (68-77°F).
- Avoid high humidity. Protect from light
- small tablet size, easy to swallow

Inactive ingredients

carnauba wax, crospovidone, D&C red no. 27 aluminum lake, dibasic calcium phosphate dihydrate, hypromellose, magnesium stearate, microcrystalline cellulose, polyethylene glycol, polysorbate 80, pregelatinized starch, stearic acid, titanium dioxide

Questions or comments?

1-800-397-9228

Gluten Free

How Supplied

They are supplied as follows:
NDC 68094-018-61
Unit Dose Packages of 100 Tablets (10×10) per Carton

Packaged by:
Precision Dose, Inc.
South Beloit, IL 61080

For inquiries call Precision Dose, Inc. at 1-800-397-9228 or email druginfo@precisiondose.com

LI1729 Rev. 10/24

PRINCIPAL DISPLAY PANEL - 25 mg Tablet Blister Pack Carton Label

PrecisionDose™

NDC 68094-018-61
Unit Dose

diphenhydrAMINE HCl
25 mg Tablets
100 Tablets
(10x10)

Each tablet contains:
Diphenhydramine Hydrochloride 25 mg
Calcium 20 mg

Gluten Free

USUAL DOSE: SEE ENCLOSED DRUG FACTS.

Store at 20-25°C (68-77°F).
Avoid high humidity. Protect from light.

Keep out of reach of children.
Hospital Use Only.

LC1733
R0

Packaged by:
Precision Dose, Inc.
South Beloit, IL 61080